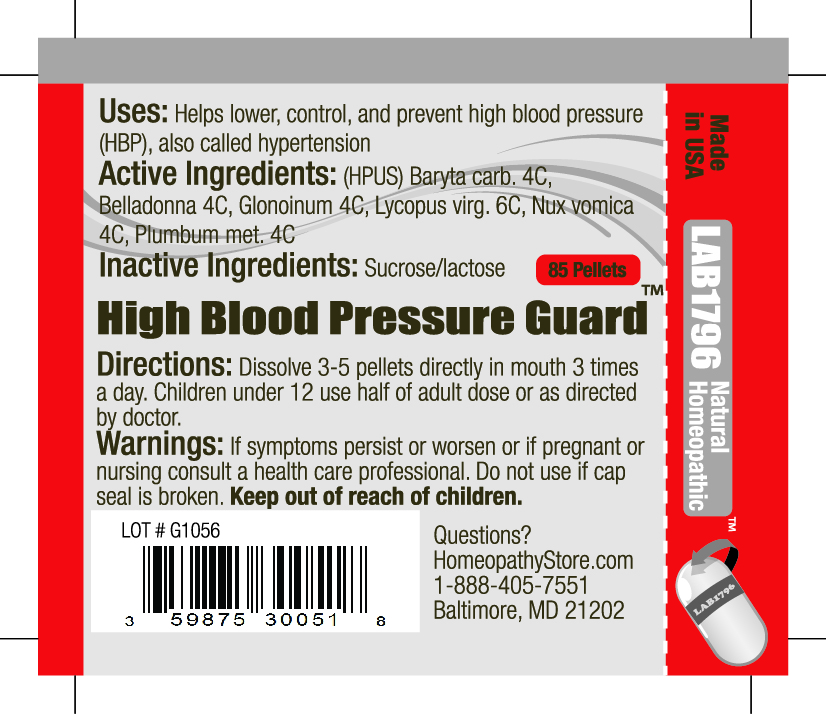 DRUG LABEL: Lab1796 High Blood Pressure Guard
NDC: 59875-3005 | Form: PELLET
Manufacturer: HomeopathyStore.com
Category: homeopathic | Type: HUMAN OTC DRUG LABEL
Date: 20101229

ACTIVE INGREDIENTS: BARIUM CARBONATE 4 [hp_C]/1 1; ATROPA BELLADONNA 4 [hp_C]/1 1; NITROGLYCERIN 4 [hp_C]/1 1; LYCOPUS VIRGINICUS 6 [hp_C]/1 1; STRYCHNOS NUX-VOMICA SEED 4 [hp_C]/1 1; LEAD 4 [hp_C]/1 1
INACTIVE INGREDIENTS: SUCROSE; LACTOSE

High Blood Pressure Guard

Uses:

Helps lower, control, and prevent high blood pressure (HBP), also called hypertension

Active Ingredients:

(HPUS) Baryta carb. 4C, Belladonna 4C, Glonoinum 4C, Lycopus virg. 6C, Nux vomica 4C, Plumbum met. 4C

Inactive Ingredients:

Sucrose/lactose

Directions:

DOSAGE AND ADMINISTRATION

Dissolve 3-5 pellets directly in mouth 3 times a day. Children under 12 use half of adult dose or as directed by doctor.

Warnings:

If symptoms persist or worsen or if pregnant or nursing consult a health care professional. Do not use if cap seal is broken.

Keep out of reach of children.